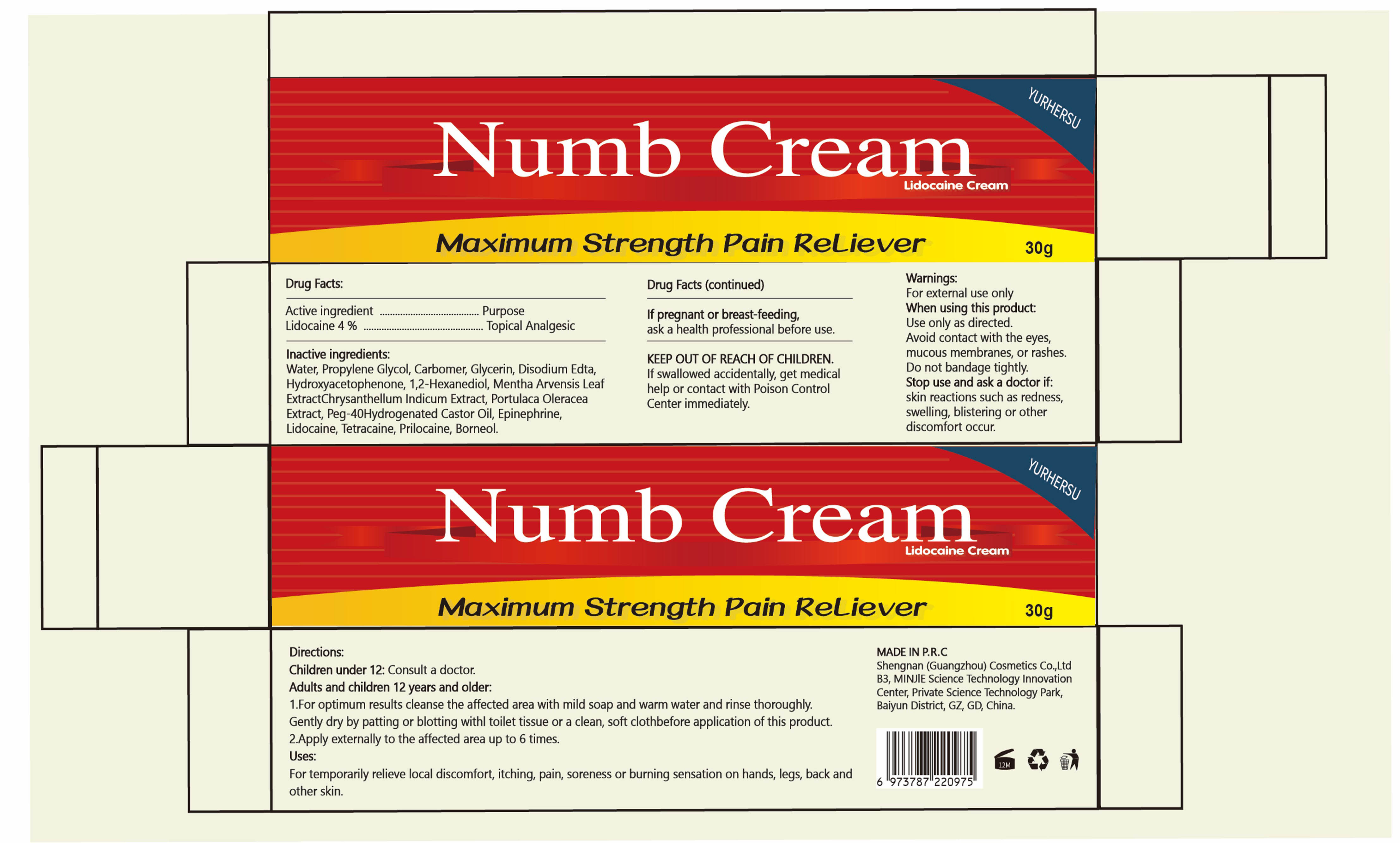 DRUG LABEL: Numb Cream
NDC: 84019-301 | Form: CREAM
Manufacturer: Shengnan (Guangzhou) Cosmetics Co., LTD
Category: otc | Type: HUMAN OTC DRUG LABEL
Date: 20240306

ACTIVE INGREDIENTS: LIDOCAINE 4 g/100 g
INACTIVE INGREDIENTS: MENTHA ARVENSIS LEAF; PORTULACA OLERACEA SEED; WATER; PRILOCAINE; HYDROXYACETOPHENONE; CHRYSANTHELLUM INDICUM TOP; CARBOMER HOMOPOLYMER, UNSPECIFIED TYPE; TETRACAINE; EPINEPHRINE; GLYCERIN; PROPYLENE GLYCOL; MAGNESIUM DISODIUM EDTA; BORNEOL; 1,2-HEXANEDIOL; PEG-40 HYDROGENATED LANOLIN

Numb Cream

Numb Cream

ACTIVE INGREDIENT

LIDOCAINE 4%

PURPOSE

Topical Analgesic

INDICATIONS AND USAGE

For temporarily relieve local discomfort, itching, pain, soreness or burning sensation on hands, legs, back and other skin.

WARNINGS

For external use only

DO NOT USE

lf pregnant or breast-feeding, ask a health professional before use.

WHEN USING

Use only as directed.
Avoid contact with the eyes,
mucous membranes, or rashes.
Do not bandage tightly.

STOP USE

skin reactions such as redness.swelling, blistering or other discomfort occur.

KEEP OUT OF REACH OF CHILDREN.
lf swallowed accidentally, get medical help or contact with Poison Control Center immediately.

DOSAGE AND ADMINISTRATION

1.For optimum results cleanse the affected area with mild soap and warm water and rinse thoroughly.
2.Apply externally to the affected area up to 6 times.

INACTIVE INGREDIENT

Water
Propylene Glycol
Carbomer
Glycerin
Disodium Edta
Hydroxyacetophenone
1.2-Hexanediol
Mentha Arvensis Leaf Extract
Chrysanthellum Indicum Extract
Portulaca Oleracea Extract
Peg-40 Hydrogenated Castor Oil
Epinephrine
Tetracaine
Prilocaine
Borneol